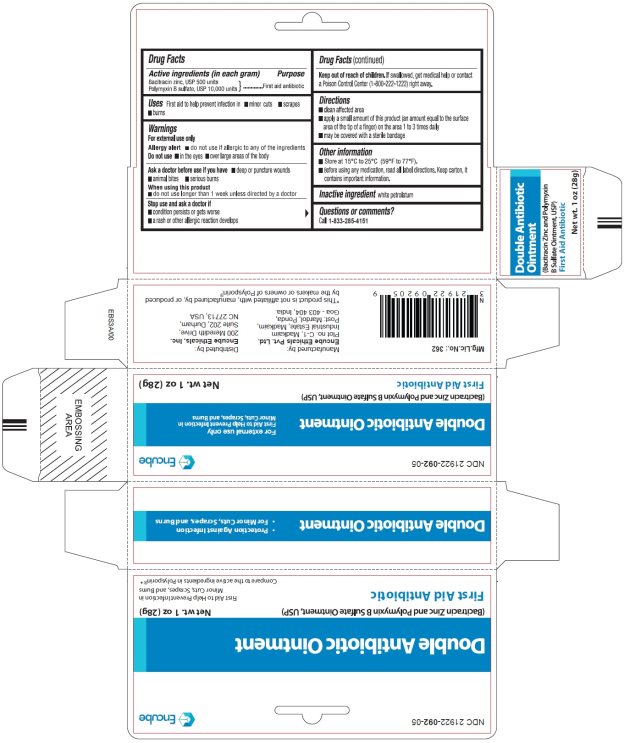 DRUG LABEL: Double Antibiotic
NDC: 21922-092 | Form: OINTMENT
Manufacturer: Encube Ethicals, Inc.
Category: otc | Type: HUMAN OTC DRUG LABEL
Date: 20250930

ACTIVE INGREDIENTS: BACITRACIN ZINC 400 [USP'U]/1 g; POLYMYXIN B SULFATE 5000 [USP'U]/1 g
INACTIVE INGREDIENTS: WHITE PETROLATUM

Double Antibiotic Ointment (Bacitracin Zinc and Polymyxin B Sulfate Ointment, USP)

Active ingredients (in each gram)

Bacitracin Zinc, USP 500 units

Polymyxin B Sulfate, USP 10,000 units

Purpose

First aid antibiotic

Uses

First aid to help prevent infection in

- minor cuts
- scrapes
- burns

Warnings

For external use only

Allergy alert ■ do not use if allergic to any of the ingredients

Do not use ■ in the eyes ■ over large areas of the body

Ask a doctor before use if you have

■ deep or puncture wounds

■ animal bites

■ serious burns

When using this product

■ do not use longer than 1 week unless directed by a doctor

Stop use and ask a doctor if

■ condition persists or gets worse

■ a rash or other allergic reaction develops

Keep out of reach of children.

If swallowed, get medical help or contact a Poison Control Center (1-800-222-1222) right away.

Directions

■ clean affected area
■ apply a small amount of this product (an amount equal to the surface area of the tip of a finger) on the area 1 to 3 times daily
■ may be covered with a sterile bandage

Other information

■ Store at 15°C to 25°C (59°F to 77°F).

■ Before using any medication, read all label directions. Keep carton, it contains important information.

Inactive ingredient

white petrolatum

Questions or comments?

Call 1-833-285-4151

PRINCIPAL DISPLAY PANEL

Double Antibiotic Ointment

First Aid Antibiotic

Net wt. 1 oz (28g)